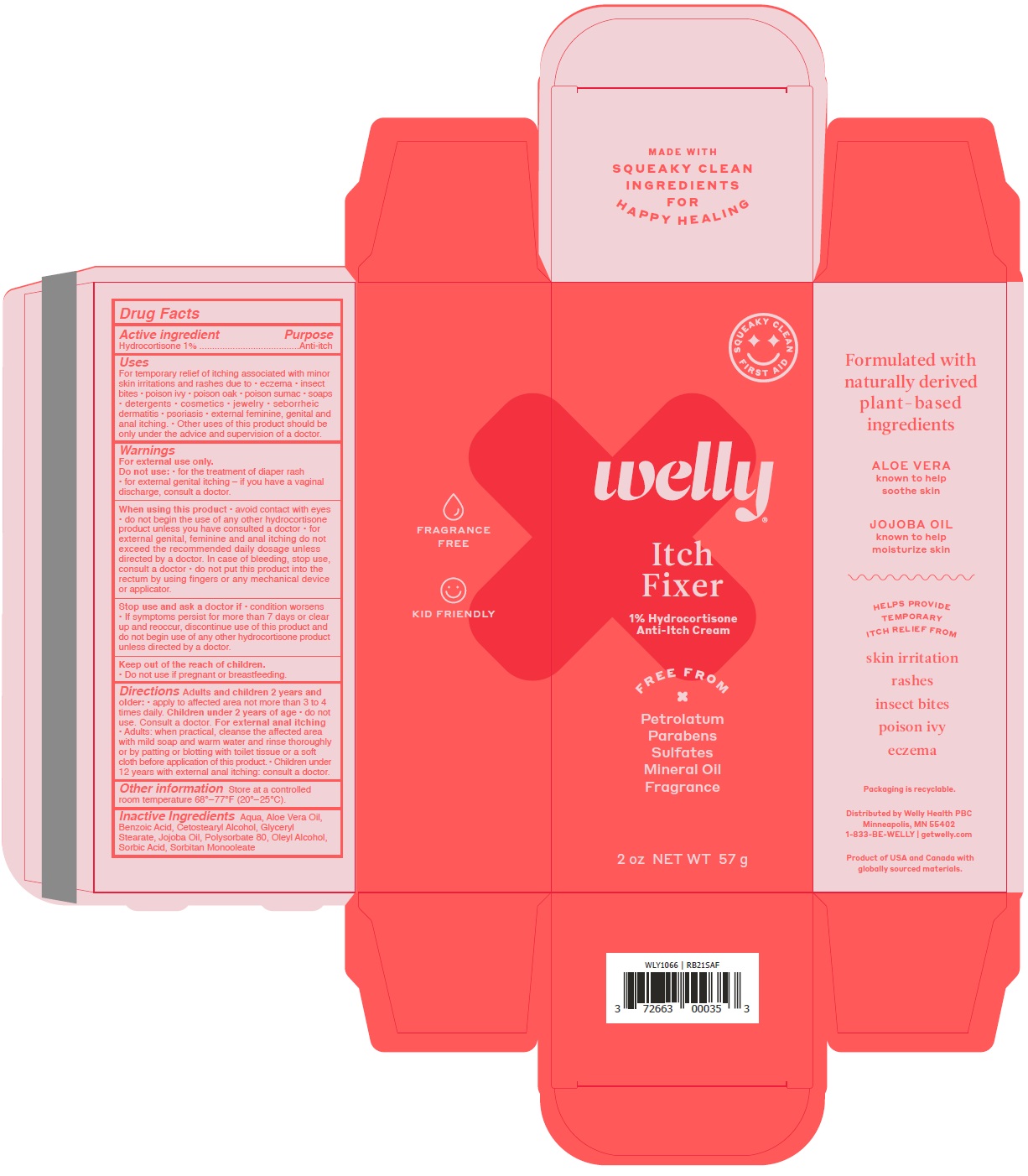 DRUG LABEL: Itch Fixer
NDC: 72663-493 | Form: CREAM
Manufacturer: Welly Health PBC
Category: otc | Type: HUMAN OTC DRUG LABEL
Date: 20210225

ACTIVE INGREDIENTS: HYDROCORTISONE 1 g/100 g
INACTIVE INGREDIENTS: WATER; ALOE VERA LEAF; BENZOIC ACID; CETOSTEARYL ALCOHOL; GLYCERYL MONOSTEARATE; JOJOBA OIL; POLYSORBATE 80; OLEYL ALCOHOL; SORBIC ACID; SORBITAN MONOOLEATE

Itch Fixer

Active ingredient

Hydrocortisone 1%

Purpose

Anti-itch

Uses

For temporary relief of itching associated with minor skin irritations and rashes due to • eczema • insect bites • poison ivy • poison oak

• poison sumac • soaps • detergents • cosmetics • jewelry • seborrheic dermatitis • psoriasis • external feminine, genital and anal itching.

• Other uses of this product should be only under the advice and supervision of a doctor.

Warnings

For external use only.

Do not use: • for the treatment of diaper rash • for external genital itching – if you have a vaginal discharge, consult a doctor.

When using this product • avoid contact with eyes • do not begin the use of any other hydrocortisone product unless

you have consulted a doctor • for external genital, feminine and anal itching do not exceed the recommended daily dosage unless directed

by a doctor. In case of bleeding, stop use, consult a doctor • do not put this product into the rectum by using fingers or any mechanical device or

applicator.

Stop use and ask a doctor if • condition worsens • If symptoms persist for more than 7 days or clear up and reoccur, discontinue use of

this product and do not begin use of any other hydrocortisone product unless directed by a doctor.

Keep out of the reach of children.

• Do not use if pregnant or breastfeeding.

Directions

Adults and children 2 years and older: • apply to affected area not more than 3 to 4 times daily.

Children under 2 years of age • do not use. Consult a doctor. For external anal itching

• Adults: when practical, cleanse the affected area with mild soap and warm water and rinse thoroughly or by patting or blotting with toilet

tissue or a soft cloth before application of this product.

• Children under 12 years with external anal itching: consult a doctor.

Other information

Store at a controlled room temperature 68°–77°F (20°–25°C).

Inactive Ingredients

Aqua, Aloe Vera Oil, Benzoic Acid, Cetostearyl Alcohol, Glyceryl Stearate, Jojoba Oil, Polysorbate 80, Oleyl Alcohol, Sorbic Acid, Sorbitan Monooleate

1% Hydrocortisone Anti-Itch Cream

FREE FROM

x

Petrolatum

Parabens

Sulfates

Mineral Oil

Fragrance

FRAGRANCE FREE

KID FRIENDLY

MADE WITH SQUEAKY CLEAN INGREDIENTS FOR HAPPY HEALING

SQUEAKY CLEAN FIRST AID

Formulated with naturally derived plant-based ingredients

ALOE VERA known to help soothe skin

JOJOBA OIL known to help moisturize skin

HELPS PROVIDE TEMPORARY ITCH RELIEF FROM

skin irritation

rashes

insect bites

poison ivy

eczema

Packaging is recyclable.

Distributed by Welly Health PBC

Minneapolis, MN 55402

1-833-BE-WELLY | getwelly.com

Product of USA and Canada with globally sourced materials.